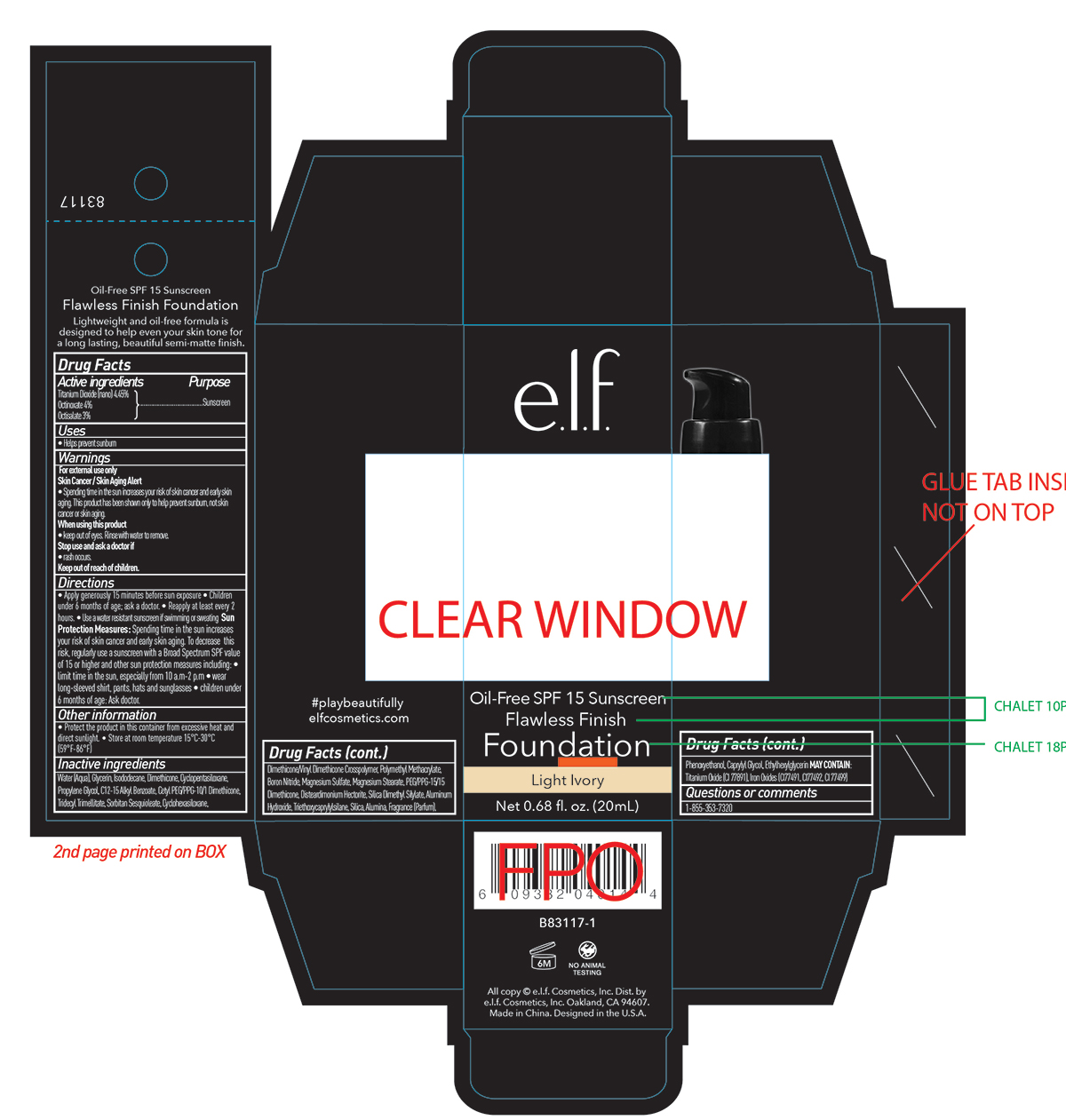 DRUG LABEL: ELF Flawless Finish Foundation Oil Free SPF 15 Sunscreen Light Ivory
NDC: 76354-631 | Form: CREAM
Manufacturer: e.l.f. Cosmetics, Inc
Category: otc | Type: HUMAN OTC DRUG LABEL
Date: 20241212

ACTIVE INGREDIENTS: TITANIUM DIOXIDE 4.45 g/100 mL; OCTISALATE 3 g/100 mL; OCTINOXATE 4 g/100 mL
INACTIVE INGREDIENTS: FERROSOFERRIC OXIDE; PROPYLENE GLYCOL; DIMETHICONE/VINYL DIMETHICONE CROSSPOLYMER (SOFT PARTICLE); TRIDECYL TRIMELLITATE; SORBITAN SESQUIOLEATE; TRIEPOXYCYCLOHEXASILANE; BORON NITRIDE; MAGNESIUM SULFATE ANHYDROUS; PEG/PPG-15/15 DIMETHICONE; DISTEARDIMONIUM HECTORITE; SILICA DIMETHYL SILYLATE; ALUMINUM HYDROXIDE; TRIETHOXYCAPRYLYLSILANE; PHENOXYETHANOL; CAPRYLYL GLYCOL; ETHYLHEXYLGLYCERIN; MAGNESIUM STEARATE; WATER; ISODODECANE; CETYL PEG/PPG-10/1 DIMETHICONE (HLB 2); GLYCERIN; DIMETHICONE; FERRIC OXIDE RED; FERRIC OXIDE YELLOW

Drug Fact

Active Ingredient:

Titanium Dioxide: 4.45%

Octinoxate: 4.0%

Octisalate: 3.0%

Purpose:

Sunscreen

Uses:

Helps prevent sunburn

Warning:

For external use only

Skin Cancer/ Skin Aging Alert:

Spending time in the sun increases your increases your risk of sking cancer or early skin aging. This product has been shown only to help prevent sunburn not sking cancer or skin aging.

When using this product:

Keep out of eyes. Rinse with water to remove.

Stop Use and Ask a Doctor if:

Rash occurs

Keep Out of Reach of Children

Directions:

For suncreen use:

Apply generally 15 min before sun exposure.

Children under six months of age: ask a doctor

Reapply at least every two hours.

Use a water resistant sunscreen if swimming or sweating

Sun Protection Measures:

Spending time in sun increases your risk of skin cancer or early skin aging. To decrease the risk, regularly use a sunscreen with broad spectrum SPF value of 15 or higher and other sun protection measures including

Other Information:

Protect this product in the container from excessive heat and direct sun

Store at room temperature 15C-30C (59F-86F)

- Limit time in the sun, especially from 10 am to 2 pm
- Wear long sleeved shirts, pants, hats, and sunglasses.
- Children under six months of age: ask a doctor

Inactive Ingredient:

Water (Aqua), Glycerin, Isododecane, Dimethicone, Cyclopentasiloxane, Propylene Glycol, C12-15 Alkyl Benzoate, Cetyl PEG/PPG-10/1 Dimethicone, Tridecyl Trimellitate, Sorbitan Sesquioleate, Cyclohexasiloxane, Dimethicone/Vinyl Dimethicone Crosspolymer, Polymethyl Methacrylate, Boron Nitride, Magnesium Sulfate, Magnesium Stearate, PEG/PPG-15/15 Dimethicone, Disteardimonium Hectorite, Silica Dimethyl Silylate, Aluminum Hydroxide, Triethoxycaprylylsilane, Silica, Alumina, Fragrance (Parfum), Phenoxyethanol, Caprylyl Glycol, EthylhexylglycerinMA

May contain:

Iron Oxides (CI 77491, CI 77492, CI 77499)